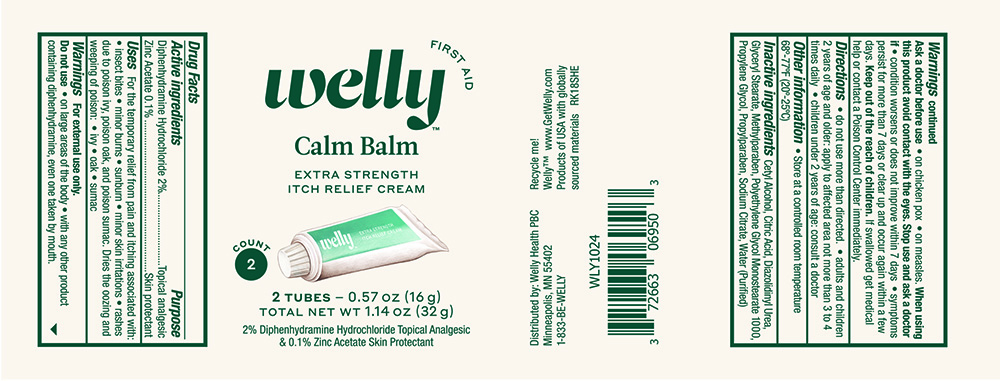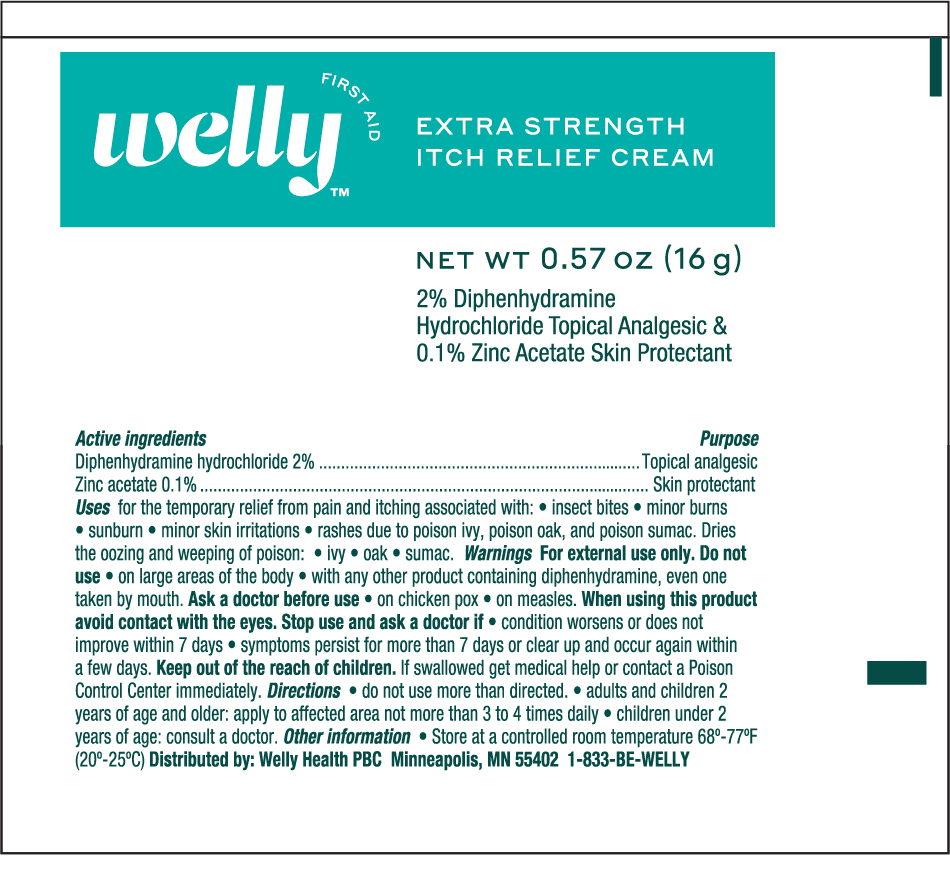 DRUG LABEL: Welly Calm Balm
NDC: 72663-069 | Form: CREAM
Manufacturer: Welly Health PBC
Category: otc | Type: HUMAN OTC DRUG LABEL
Date: 20190209

ACTIVE INGREDIENTS: DIPHENHYDRAMINE HYDROCHLORIDE 20 mg/1 g; ZINC ACETATE 1 mg/1 g
INACTIVE INGREDIENTS: CETYL ALCOHOL; DIAZOLIDINYL UREA; METHYLPARABEN; GLYCERYL STEARATE SE; PROPYLENE GLYCOL; PROPYLENE GLYCOL MONOSTEARATE; PROPYLPARABEN; WATER; CITRIC ACID MONOHYDRATE; SODIUM CITRATE

Active ingredients

Diphenhydramine hydrochloride 2%

Zinc Acetate 0.1%

Purpose

Topical analgesic

Skin protectant

Uses

For temporary relief from pain and itching associated with :

- insect bites
- minor burns
- sunburn
- minor skin irritations
- rashes due to poison ivy, poison oak, and poison sumac

Dries the oozing and weeping of poison

- ivy
- oak
- sumac

Warnings

For external use only

Do not use

- on large areas of the body
- with any other product containing diphenhydramine , even one taken by the mouth.

Ask a Doctor before use

- on chicken pox
- on measles

When using this product avoid contact with eyes.

Stop use and ask a doctor if

- conditions worsen or does not improve within 7 days
- symptoms persist for more than 7 days or clear up and occur agian within a few days

Keep this and all drugs out of the reach of children.

If swallowed get medical help or contact a Poison Control Center immediately.

Directions

- do not use more than directed
- adults and children 2 years of age and older; apply to affected areas not more than 3 to 4 times daily
- children under 2 years of age , consult a doctor

Other Information

- Store at controlled room temperature 20°-25°C (68° - 77°F)
- Close the cap tightly after use

Inactive ingredients

Cetyl Alcohol, Citric Acid, Diazolldinyl Urea, Glyceryl Sterate, Methylparaben, Polyethylene Glycol Monosterate 1000, Propylene Glycol, Propylparaben, Sodium Citrate , Purified Water

Principal Display Panel .57 oz Tube

Welly First aid NDC 72663-069-59

Extra Strength ANTI -ITCH cream

2% Diphenhydramine HCL topical analgesic

0.1% Zinc Acetate skin protectant

NET WT 0.57 oz (16g)

Principal Display Panel -Can

Welly Calm Balm First aid NDC 72663-069-59

Extra Strength ANTI -ITCH cream

2% Diphenhydramine HCL topical analgesic

0.1% Zinc Acetate skin protectant

NET WT 0.57 oz (16g)

2- Tubes 1.14 oz (32g)